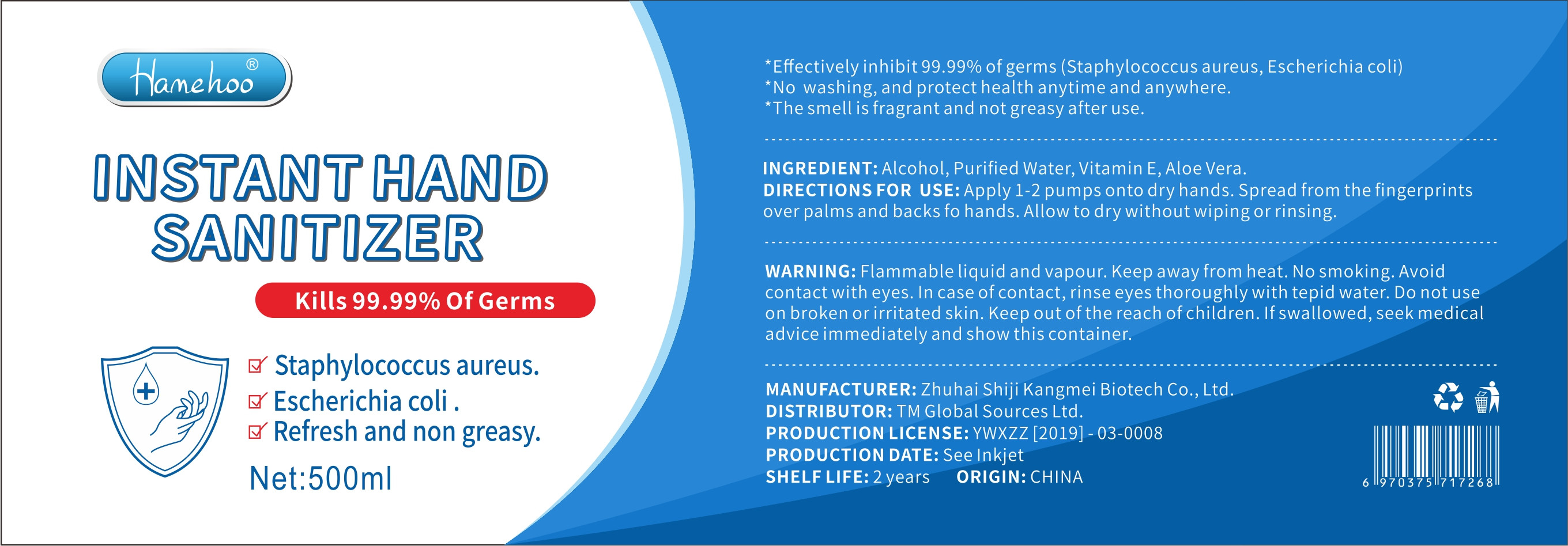 DRUG LABEL: INSTANT HAND SANITIER
NDC: 41747-001 | Form: LIQUID
Manufacturer: Zhuhai Shiji Kangmei Biotech Co., Ltd.
Category: otc | Type: HUMAN OTC DRUG LABEL
Date: 20200429

ACTIVE INGREDIENTS: ALCOHOL 375 mL/500 mL
INACTIVE INGREDIENTS: GLYCERIN; ALOE; WATER; POLYACRYLIC ACID (250000 MW)

DOSAGE AND ADMINISTRATION

Flammable liquid and vapour. Keep away from heat.

INACTIVE INGREDIENT

Purified water

vitamin E

Aloe Vera

Glycerin

Carbomer

INDICATIONS AND USAGE

Apply 1-2 pumps onto dry hands. Spread from the fingerprints over palms and backs fo hands. Allow to dry without wiping or rinsing.

ACTIVE INGREDIENT

Ethylalcohol

keep out of reach of children

PURPOSE

Disinfection
Sterilization
No Rinseing

WARNINGS

Flammable liquid and vapour. Keep away from heat. No smoking. Avoid contact with eyes. In case of contact, rinse eyes thoroughly with tepid water. Do not use on broken or irritated skin. Keep out of the reach of children. If swallowed, seek medical advice immediately and show this container.